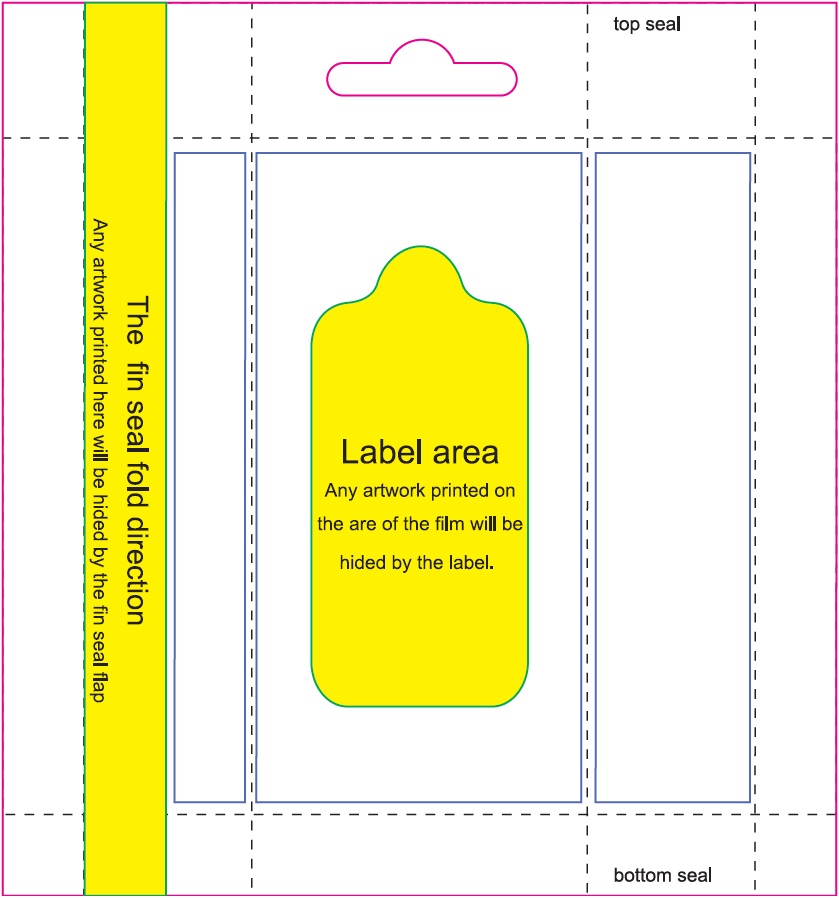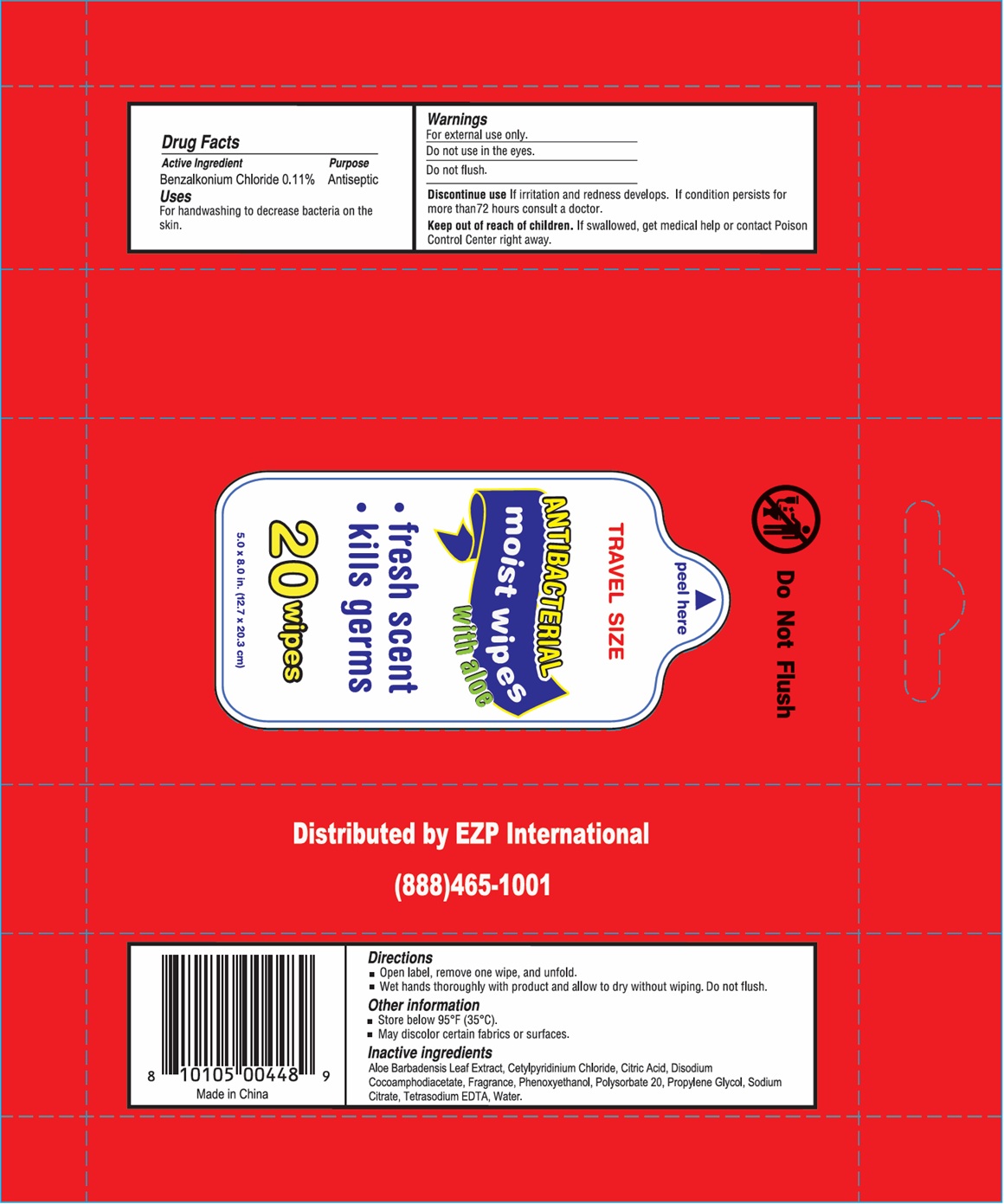 DRUG LABEL: EZ-448 Antibacterial Moist Hand
NDC: 69446-200 | Form: SWAB
Manufacturer: Ez Products Of South Florida, LLC
Category: otc | Type: HUMAN OTC DRUG LABEL
Date: 20250924

ACTIVE INGREDIENTS: BENZALKONIUM CHLORIDE 0.11 g/100 g
INACTIVE INGREDIENTS: PHENOXYETHANOL; DISODIUM COCOAMPHODIACETATE; EDETATE SODIUM; POLYSORBATE 20; ALOE VERA LEAF; CITRIC ACID MONOHYDRATE; SODIUM CITRATE; WATER; PROPYLENE GLYCOL

EZ-448 Antibacterial Moist Hand Wipe

Active Ingredient

Benzalkonium Chloride 0.11%

Purpose

Antiseptic

Uses

For handwashing to decrease bacteria on the skin.

Warnings

For external use only.

Do not use

in the eyes.

Do not flush.

Discontinue use if

irritation and redness develops. If condition persists for more than 72 hours consult a doctor.

Keep out of reach of children.

If swallowed, get medical help or contact Poison Control Center right away.

Directions

- Open label, remove one wipe, and unfold.
- Wet hands thoroughly with product and allow to dry without wiping. Do not flush.

Other information

- Store below 95°F (35°C).
- May discolor certain fabrics or surfaces.

Inactive ingredients

Aloe Barbadensis Leaf Extract, Cetylpyridinium Chloride, Citric Acid, Disodium Cocoamphodiacetate, Fragrance, Phenoxyethanol, Polysorbate 20, Propylene Glycol, Sodium Citrate, Tetrasodium EDTA, Water